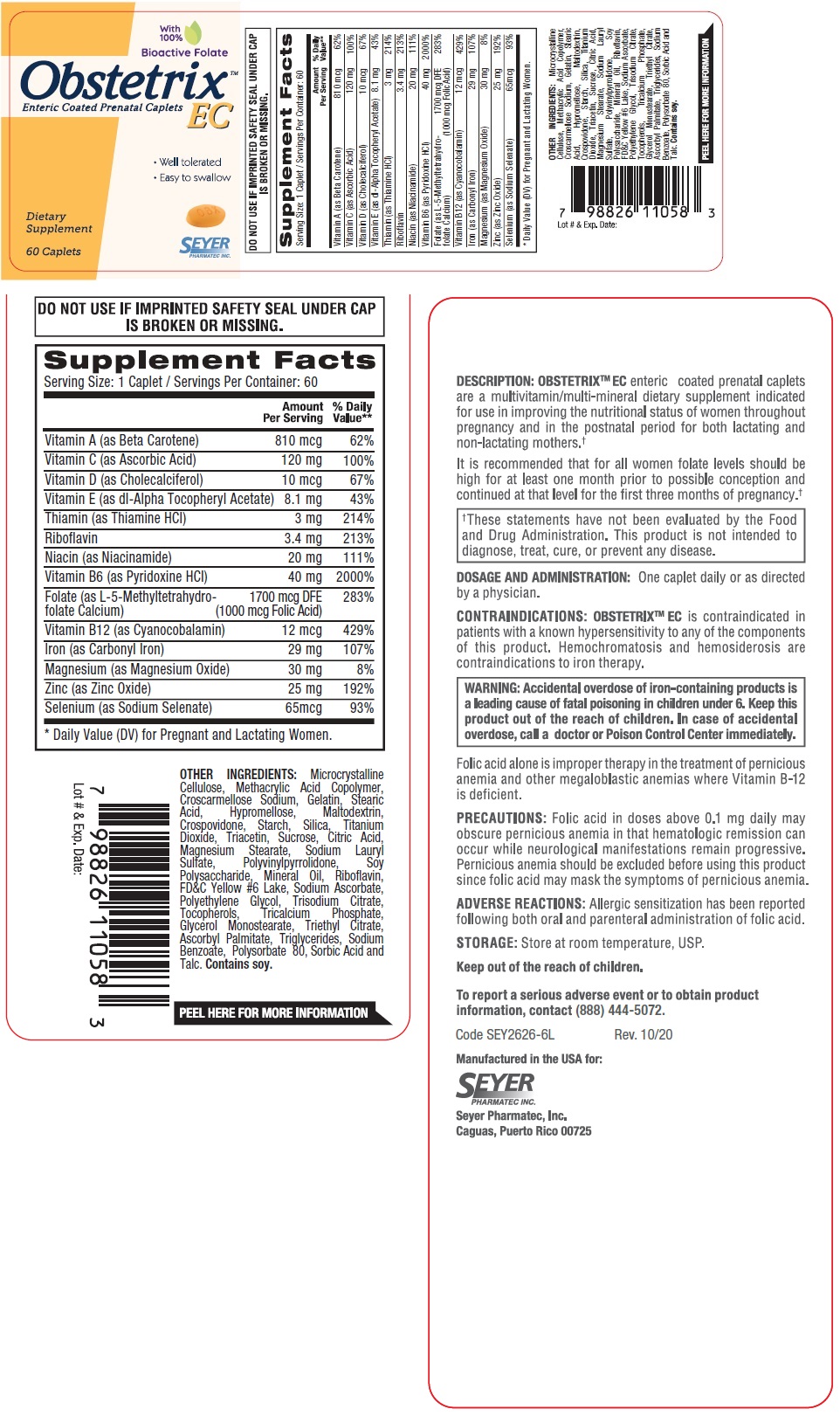 DRUG LABEL: Obstetrix EC
NDC: 11026-2632 | Form: TABLET
Manufacturer: Seyer Pharmatec, Inc.
Category: other | Type: DIETARY SUPPLEMENT
Date: 20230214

ACTIVE INGREDIENTS: BETA CAROTENE 810 ug/1 1; ASCORBIC ACID 120 mg/1 1; CHOLECALCIFEROL 10 ug/1 1; .ALPHA.-TOCOPHEROL ACETATE, DL- 8.1 mg/1 1; THIAMINE HYDROCHLORIDE 3 mg/1 1; RIBOFLAVIN 3.4 mg/1 1; NIACINAMIDE 20 mg/1 1; PYRIDOXINE HYDROCHLORIDE 40 mg/1 1; LEVOMEFOLATE CALCIUM 1700 ug/1 1; CYANOCOBALAMIN 12 ug/1 1; IRON 29 mg/1 1; MAGNESIUM OXIDE 30 mg/1 1; ZINC OXIDE 25 mg/1 1; SODIUM SELENATE 65 ug/1 1
INACTIVE INGREDIENTS: MICROCRYSTALLINE CELLULOSE; METHACRYLIC ACID - METHYL METHACRYLATE COPOLYMER (1:1); CROSCARMELLOSE SODIUM; GELATIN, UNSPECIFIED; STEARIC ACID; HYPROMELLOSE, UNSPECIFIED; MALTODEXTRIN; CROSPOVIDONE, UNSPECIFIED; STARCH, CORN; SILICON DIOXIDE; TITANIUM DIOXIDE; TRIACETIN; SUCROSE; CITRIC ACID MONOHYDRATE; MAGNESIUM STEARATE; SODIUM LAURYL SULFATE; POVIDONE K60; SOYBEAN COTYLEDON CELL WALL POLYSACCHARIDES; MINERAL OIL; FD&C YELLOW NO. 6; SODIUM ASCORBATE; POLYETHYLENE GLYCOL, UNSPECIFIED; SODIUM CITRATE, UNSPECIFIED FORM; TOCOPHEROL; TRICALCIUM PHOSPHATE; GLYCERYL MONOSTEARATE; TRIETHYL CITRATE; ASCORBYL PALMITATE; MEDIUM-CHAIN TRIGLYCERIDES; SODIUM BENZOATE; POLYSORBATE 80; SORBIC ACID; TALC

Obstetrix™ EC

STATEMENT OF IDENTITY

Supplement Facts
Serving Size: 1 Caplet / Servings Per Container: 60
 | Amount | % Daily
 | Per Serving | Value**
Vitamin A (as Beta Carotene) | 810 mcg | 62%
Vitamin C (as Ascorbic Acid) | 120 mg | 100%
Vitamin D (as Cholecalciferol) | 10 mcg | 67%
Vitamin E (as dl-Alpha Tocopheryl Acetate) | 8.1 mg | 43%
Thiamin (as Thiamine HCl) | 3 mg | 214%
Riboflavin | 3.4 mg | 213%
Niacin (as Niacinamide) | 20 mg | 111%
Vitamin B6 (as Pyridoxine HCl) | 40 mg | 2000%
Folate (as L-5-Methyltetrahydrofolate Calcium) | 1700 mcg DFE | 283%
 | (1000 mcg Folic Acid)
Vitamin B12 (as Cyanocobalamin) | 12 mcg | 429%
Iron (as Carbonyl Iron) | 29 mg | 107%
Magnesium (as Magnesium Oxide) | 30 mg | 8%
Zinc (as Zinc Oxide) | 25 mg | 192%
Selenium (as Sodium Selenate) | 65mcg | 93%
* Daily Value (DV) for Pregnant and Lactating Women.

OTHER INGREDIENTS:

Microcrystalline Cellulose, Methacrylic Acid Copolymer, Croscarmellose Sodium, Gelatin, Stearic Acid, Hypromellose, Maltodextrin, Crospovidone, Starch, Silica, Titanium Dioxide, Triacetin, Sucrose, Citric Acid, Magnesium Stearate, Sodium Lauryl Sulfate, Polyvinylpyrrolidone, Soy Polysaccharide, Mineral Oil, Riboflavin, FD&C Yellow #6 Lake, Sodium Ascorbate, Polyethylene Glycol, Trisodium Citrate, Tocopherols, Tricalcium Phosphate, Glycerol Monostearate, Triethyl Citrate, Ascorbyl Palmitate, Triglycerides, Sodium Benzoate, Polysorbate 80, Sorbic Acid and Talc. Contains soy.

DESCRIPTION:

OBSTETRIX™ EC enteric coated prenatal caplets are a multivitamin/multi-mineral dietary supplement indicated for use in improving the nutritional status of women throughout pregnancy and in the postnatal period for both lactating and non-lactating mothers.†

It is recommended that for all women folate levels should be high for at least one month prior to possible conception and continued at that level for the first three months of pregnancy.†

†These statements have not been evaluated by the Food and Drug Administration. This product is not intended to diagnose, treat, cure, or prevent any disease.

DOSAGE AND ADMINISTRATION:

One caplet daily or as directed by a physician.

CONTRAINDICATIONS:

OBSTETRIX™ EC is contraindicated in patients with a known hypersensitivity to any of the components of this product. Hemochromatosis and hemosiderosis are contraindications to iron therapy.

WARNINGS

WARNING: Accidental overdose of iron-containing products is a leading cause of fatal poisoning in children under 6. Keep this product out of the reach of children. In case of accidental overdose, call a doctor or Poison Control Center immediately.

Folic acid alone is improper therapy in the treatment of pernicious anemia and other megaloblastic anemias where Vitamin B-12 is deficient.

PRECAUTIONS:

Folic acid in doses above 0.1 mg daily may obscure pernicious anemia in that hematologic remission can occur while neurological manifestations remain progressive. Pernicious anemia should be excluded before using this product since folic acid may mask the symptoms of pernicious anemia.

ADVERSE REACTIONS:

Allergic sensitization has been reported following both oral and parenteral administration of folic acid.

STORAGE:

Store at room temperature, USP.

Keep out of the reach of Children.

To report a serious adverse event or to obtain product information, contact (888) 444-5072.

Manufactured in the USA for:
Seyer Pharmatec, Inc.
Caguas, Puerto Rico 00725

DO NOT USE IF IMPRINTED SAFETY SEAL UNDER CAP IS BROKEN OR MISSING.

HEALTH CLAIM

Dietary Supplement

Enteric Coated Prenatal Caplets

with 100% Bioactive Folate

• Well tolerated
• Easy to swallow